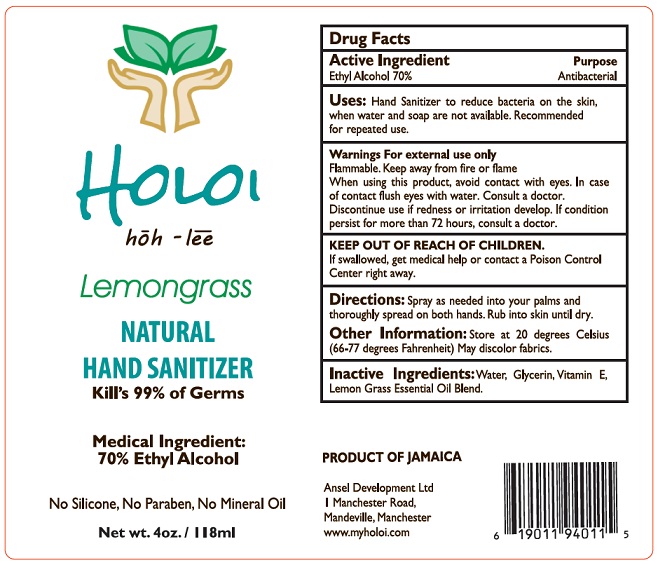 DRUG LABEL: HOLOI
NDC: 78483-001 | Form: LIQUID
Manufacturer: LIFEN1 LLC
Category: otc | Type: HUMAN OTC DRUG LABEL
Date: 20200602

ACTIVE INGREDIENTS: ALCOHOL 80 mL/100 mL
INACTIVE INGREDIENTS: GLYCERIN; .ALPHA.-TOCOPHEROL; WATER; WEST INDIAN LEMONGRASS OIL

Active Ingredient

Ethyl Alcohol 70% v/v.

Purpose

Antibacterial

Uses

Hand Sanitizer to reduce bacteria on the skin, when water and soap are not available. Recommended for repeated use.

Warnings

For External Use Only.

Flammable. Keep away from fire or flame.

When using this product, avoid contact with eyes. In case of contact, flush eyes with water. Consult a doctor.

Discontinue use if redness or irritation develop. If condition persist form more than 72 hours, consult a doctor.

Keep out of reach of children. If swallowed, get medical help or contact a Poison Control Center right away.

Directions

Spray as much into your pals and thoroughly spread on both hands. Rub into skin until dry.

Other information

Store at 20 degrees Celsius (66-77 degrees Fahrenheit).

May discolor fabrics.

Inactive ingredients

Water, Glycerin, Vitamin E, Lemon Grass Essential Oil Blend.